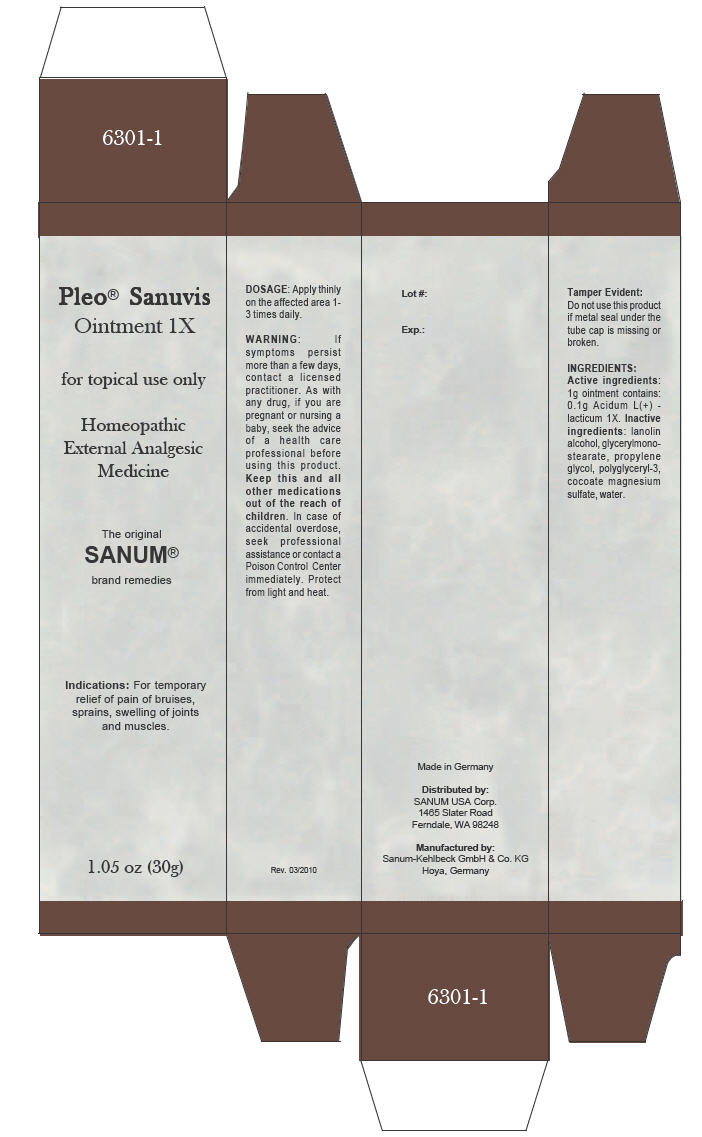 DRUG LABEL: Pleo Sanuvis
NDC: 60681-6301 | Form: OINTMENT
Manufacturer: Sanum Kehlbeck GmbH & Co. KG
Category: homeopathic | Type: HUMAN OTC DRUG LABEL
Date: 20100604

ACTIVE INGREDIENTS: lactic acid, l- 1 [hp_X]/30 g
INACTIVE INGREDIENTS: glyceryl monostearate; lanolin alcohols; water

Pleo® Sanuvis
Ointment 1X

for topical use only

Homeopathic External Analgesic Medicine

1.05 oz (30g)

Indications

For temporary relief of pain of bruises, sprains, swelling of joints and muscles.

DOSAGE

Apply thinly on the affected area 1-3 times daily.

WARNING

If symptoms persist more than a few days, contact a licensed practitioner. As with any drug, if you are pregnant or nursing a baby, seek the advice of a health care professional before using this product.

KEEP OUT OF REACH OF CHILDREN

Keep this and all other medications out of the reach of children. In case of accidental overdose, seek professional assistance or contact a Poison Control Center immediately.

STORAGE AND HANDLING

Protect fom light and heat.

Tamper Evident

Do not use this product if metal seal under the tube cap is missing or broken.

INGREDIENTS

Active ingredients

1g ointment contains: 0.1g Acidum L(+) - lacticum 1X.

Inactive ingredients

lanolin alcohol, glycerylmonostearate, propylene glycol, polyglyceryl-3, cocoate magnesium sulfate, water.

Made in Germany

Distributed by:
SANUM USA Corp.
1465 Slater Road
Ferndale, WA 98248

Manufactured by:
Sanum-Kehlbeck GmbH & Co. KG
Hoya, Germany

Rev. 03/2010

PRINCIPAL DISPLAY PANEL - 30g Tube Carton

Pleo® Sanuvis
Ointment 1X

for topical use only

Homeopathic
External Analgesic
Medicine

The original
SANUM®
brand remedies

Indications: For temporary
relief of pain of bruises,
sprains, swelling of joints
and muscles.

1.05 oz (30g)